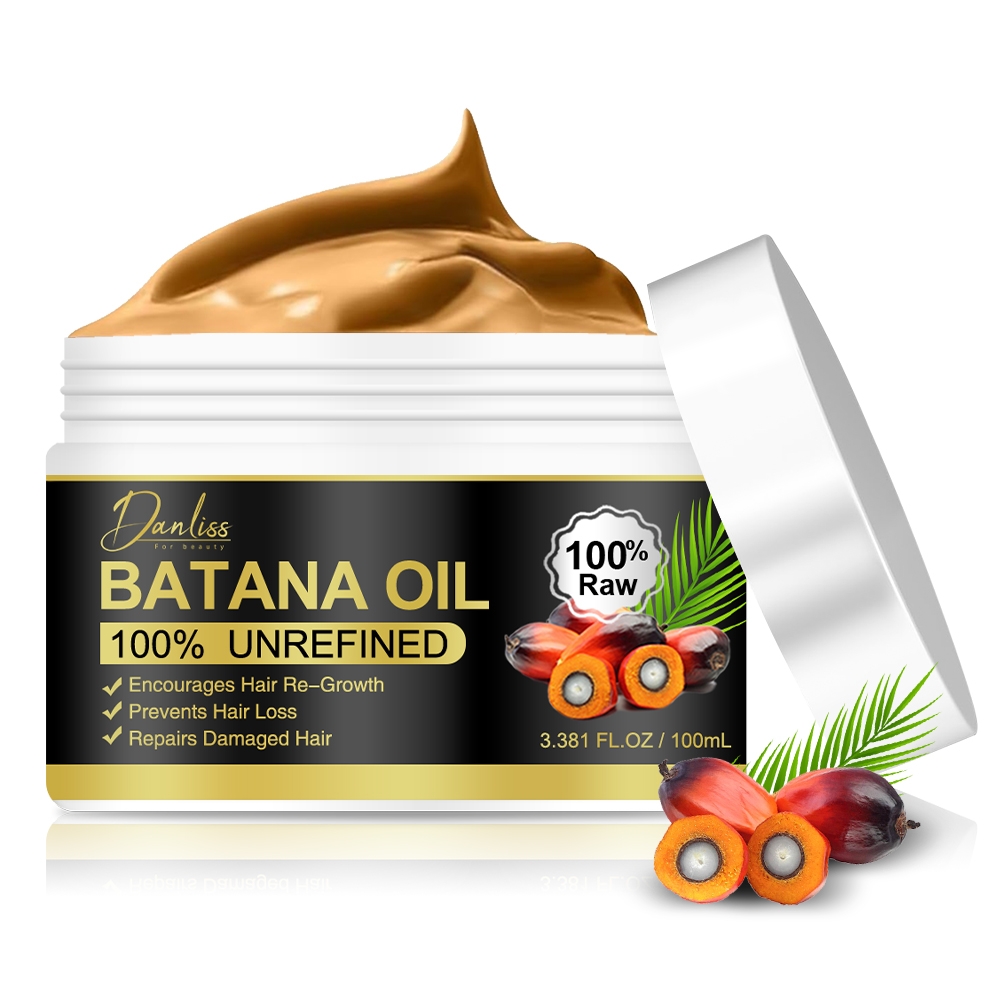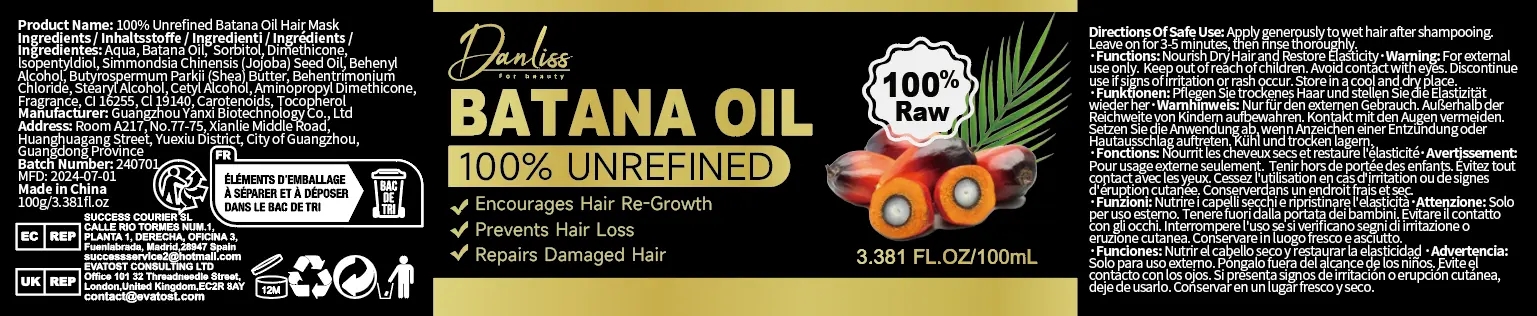 DRUG LABEL: 100% Unrefined Batana Oil Hair Mask
NDC: 84025-220 | Form: CREAM
Manufacturer: Guangzhou Yanxi Biotechnology Co., Ltd
Category: otc | Type: HUMAN OTC DRUG LABEL
Date: 20241018

ACTIVE INGREDIENTS: SORBITOL 5 mg/100 mL; DIMETHICONE 3 mg/100 mL
INACTIVE INGREDIENTS: WATER

DOSAGE AND ADMINISTRATION

use as a normal hair cream

WARNINGS

keep out of children

INACTIVE INGREDIENT

AQUA

INDICATIONS AND USAGE

For daily hair care

keep out of children

PURPOSE

strong and nourishing hair